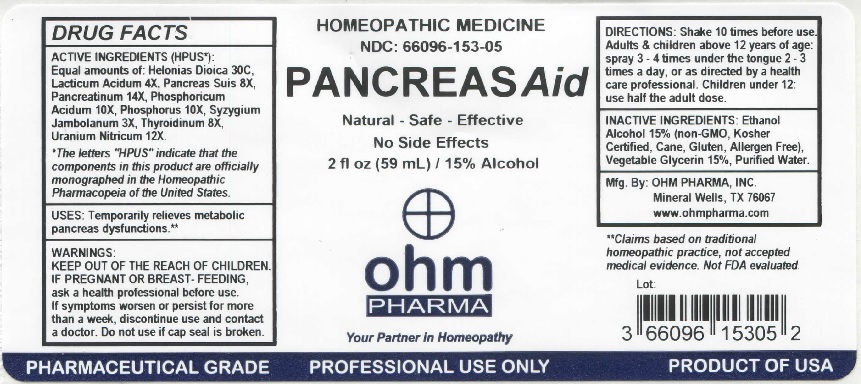 DRUG LABEL: OHM Pancreas Aid
NDC: 66096-153 | Form: LIQUID
Manufacturer: OHM PHARMA INC.
Category: homeopathic | Type: HUMAN OTC DRUG LABEL
Date: 20211229

ACTIVE INGREDIENTS: CHAMAELIRIUM LUTEUM ROOT 30 [hp_C]/59 mL; LACTIC ACID, DL- 4 [hp_X]/59 mL; SUS SCROFA PANCREAS 8 [hp_X]/59 mL; PANCRELIPASE 14 [hp_X]/59 mL; PHOSPHORIC ACID 10 [hp_X]/59 mL; PHOSPHORUS 10 [hp_X]/59 mL; SYZYGIUM CUMINI SEED 3 [hp_X]/59 mL; THYROID, UNSPECIFIED 8 [hp_X]/59 mL; URANYL NITRATE HEXAHYDRATE 12 [hp_X]/59 mL
INACTIVE INGREDIENTS: ALCOHOL; GLYCERIN; WATER

OHM Pancreas Aid

ACTIVE INGREDIENT

ACTIVE INGREDIENTS (HPUS*): Equal amounts of: Helonias Dioica 30C, Lacticum Acidum 4X, Pancreas Suis 8X, Pancreatinum 14X, Phosphoricum Acidum 10X, Phosphorus 10X, Syzygium Jambolanum 3X, Thyroidinum 8X, Uranium Nitricum 12X.

*The letters "HPUS" indicate that the components in this product are officially monographed in the Homeopathic Pharmacopeia of the United States.

INDICATIONS AND USAGE

USES: Temporarily relieves metabolic pancreas dysfunctions.**

**Claims based on traditional homeopathic practice, not accepted medical evidence. Not FDA evaluated.

WARNINGS

WARNINGS: IF PREGNANT OR BREAST-FEEDING, ask a health professional before use. If symptoms worsen or persist for more than a week, discontinue use and contact a doctor.

- KEEP OUT OF REACH OF CHILDREN.

DOSAGE AND ADMINISTRATION

DIRECTIONS: Shake 10 times before use. Adults & children above 12 years of age: spray 3-4 times under the tongue 2-3 times a day, or as directed by a health care professional. Children under 12 years: use half the adult dose.

Do not use if cap seal is broken.

INACTIVE INGREDIENT

INACTIVE INGREDIENTS: Ethanol Alcohol 15% (non-GMO, Kosher Certified, Cane, Gluten, Allergen Free), Vegetable Glycerin 15%, Purified Water.

QUESTIONS

Mfg. By: OHM PHARMA, INC. Mineral Wells, TX 76067

www.ohmpharma.com

PACKAGE LABEL

HOMEOPATHIC MEDICINE

NDC: 66096-153-05

PANCREAS Aid

Natural - Safe - Effective

No Side Effects

2 fl oz (59 mL) / 15% Alcohol

PURPOSE

Relieves metabolic pancreas dysfunctions.